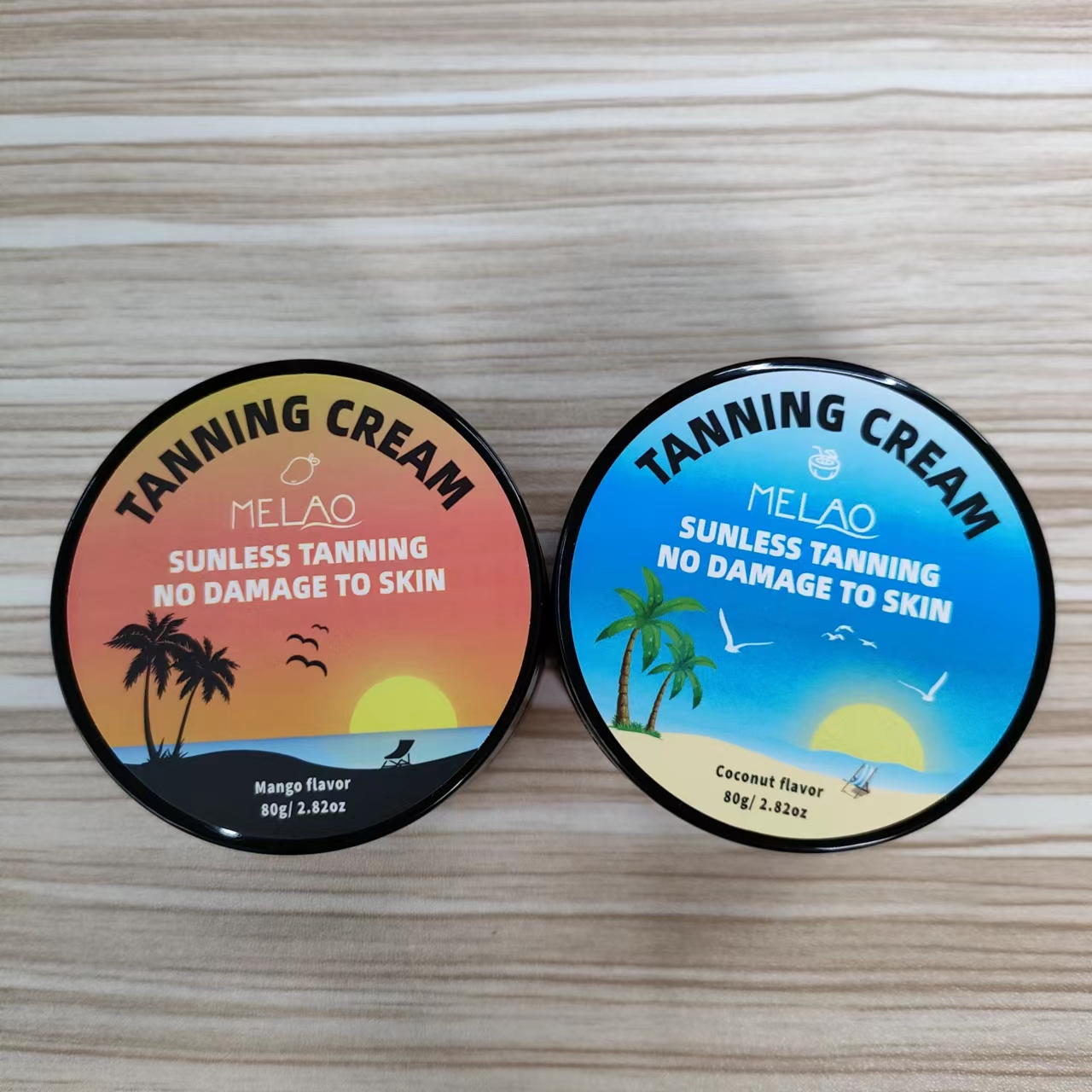 DRUG LABEL: MELAO Tanning Cream
NDC: 74458-552 | Form: CREAM
Manufacturer: Guangzhou Yilong Cosmetics Co.,Ltd.
Category: otc | Type: HUMAN OTC DRUG LABEL
Date: 20241027

ACTIVE INGREDIENTS: COCOS NUCIFERA (COCONUT) OIL 5 g/100 g; BUTYROSPERMUM PARKII (SHEA) OIL 5 g/100 g; OLEA EUROPAEA (OLIVE) FRUIT OIL 5 g/100 g
INACTIVE INGREDIENTS: CETEARYL ALCOHOL; WATER; ETHYLHEXYLGLYCERIN; XANTHAN GUM; PHENOXYETHANOL; PARFUMIDINE

MELAO TANNING CREAM

ACTIVE INGREDIENT

Olea Europaea (Olive) Fruit Oil

Butyrospermum Parkii (Shea) Oil

Cocos Nucifera (Coconut) Oil

INACTIVE INGREDIENT

Water

Cetearyl Alcohol

Xanthan Gum

Phenoxyethanol

Ethylhexylglycerin

Parfum

PURPOSE

Sunless Tanning.

INDICATIONS AND USAGE

Apply an appropriate amount evenly on the skin and massage until absorbed. Better results in four hours or more.

DOSAGE AND ADMINISTRATION

Apply an appropriate amount evenly on the skin and massage until absorbed. Better results in four hours or more.

WARNINGS

For external use only.

Stop use and ask a doctor if rash occurs.

Do not use on damaged or broken skin.

When using this product keep out of eyes. Rinse with water to remove.

Keep out of reach of children. If swallowed, get medical help or contact a Poison Control Center right away.